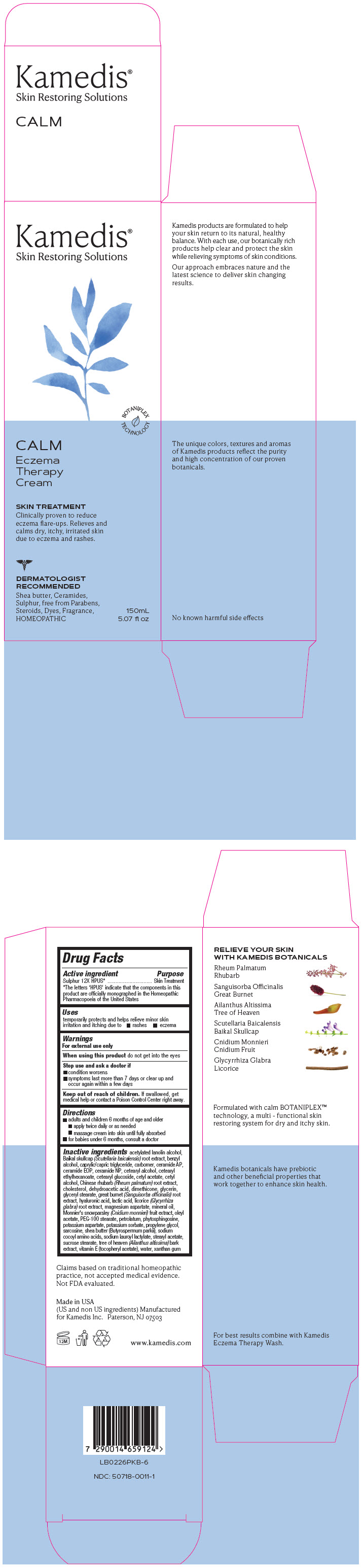 DRUG LABEL: Calm Eczema Therapy Cream
NDC: 50718-0011 | Form: CREAM
Manufacturer: Kamedis
Category: homeopathic | Type: HUMAN OTC DRUG LABEL
Date: 20240212

ACTIVE INGREDIENTS: SULFUR 12 [hp_X]/1 mL
INACTIVE INGREDIENTS: ACETYLATED LANOLIN ALCOHOLS; SCUTELLARIA BAICALENSIS ROOT; BENZYL ALCOHOL; MEDIUM-CHAIN TRIGLYCERIDES; CARBOMER HOMOPOLYMER, UNSPECIFIED TYPE; CERAMIDE AP; CERAMIDE 1; CERAMIDE NP; CETOSTEARYL ALCOHOL; CETEARYL ETHYLHEXANOATE; CETEARYL GLUCOSIDE; CETYL ACETATE; CETYL ALCOHOL; RHEUM PALMATUM ROOT; CHOLESTEROL; DEHYDROACETIC ACID; DIMETHICONE; GLYCERIN; GLYCERYL STEARATE SE; SANGUISORBA OFFICINALIS ROOT; HYALURONIC ACID; LACTIC ACID, UNSPECIFIED FORM; GLYCYRRHIZA GLABRA; MAGNESIUM ASPARTATE; CNIDIUM MONNIERI FRUIT; MINERAL OIL; 9-OCTADECENYL ACETATE, (9Z)-; PEG-100 STEARATE; PETROLATUM; PHYTOSPHINGOSINE; POTASSIUM ASPARTATE; POTASSIUM SORBATE; PROPYLENE GLYCOL; SARCOSINE; SHEA BUTTER; SODIUM LAUROYL LACTYLATE; STEARYL ACETATE; SUCROSE STEARATE; AILANTHUS ALTISSIMA BARK; .ALPHA.-TOCOPHEROL ACETATE; WATER; XANTHAN GUM; sodium cocoyl wheat amino acids

Calm Eczema Therapy Cream

Drug Facts

Active ingredient

Sulphur 12X HPUS*
* The letters 'HPUS' indicate that the components in this product are officially monographed in the Homeopathic Pharmacopoeia of the United States

Purpose

Skin Treatment

Uses

• temporarily protects and helps relieve minor skin irritation and itching due to:

- rashes
- eczema

Warnings

For external use only

When using this product

- do not get into eyes

Stop use and ask a doctor if

- condition worsens
- symptoms last more than 7 days or clear up and occur again within a few days

Keep out of reach of children

- If swallowed, get medical help or contact a Poison Control Center right away

Directions

- adults and children 6 months of age and older
  • apply twice daily or as needed
  • massage cream into skin until fully absorbed
- for babies under 6 months, consult a doctor

Inactive ingredients

acetylated lanolin alcohol, Baikal skullcap (Scutellaria baicalensis) root extract, benzyl alcohol, caprylic/capric triglyceride, carbomer, ceramide AP, ceramide EOP, ceramide NP, cetearyl alcohol, cetearyl ethylhexanoate, cetearyl glucoside, cetyl acetate, cetyl alcohol, Chinese rhubarb (Rheum palmatum) root extract, cholesterol, dehydroacetic acid, dimethicone, glycerin, glyceryl stearate, great burnet (Sanguisorba officinalis) root extract, hyaluronic acid, lactic acid, licorice (Glycyrrhiza glabra) root extract, magnesium aspartate, mineral oil, Monnier's snowparsley (Cnidium monnieri) fruit extract, oleyl acetate, PEG-100 stearate, petrolatum, phytosphingosine, potassium aspartate, potassium sorbate, propylene glycol, sarcosine, shea butter (Butyrospermum parkii), sodium cocoyl amino acids, sodium lauroyl lactylate, stearyl acetate, sucrose stearate, tree of heaven (Ailanthus altissima) bark extract, vitamin E (tocopheryl acetate), water, xanthan gum

Claims based on traditional homeopathic practice, not accepted medical evidence. Not FDA evaluated.

Made in USA
(US and non US ingredients) Manufactured
for Kamedis Inc. Paterson, NJ 07503

www.kamedis.com

PRINCIPAL DISPLAY PANEL - 150 mL Tube Carton

Kamedis®
Skin Restoring Solutions

BOTANIPLEX
TECHNOLOGY

CALM

Eczema
Therapy
Cream

SKIN TREATMENT
Clinically proven to reduce
eczema flare-ups. Relieves and
calms dry, itchy, irritated skin
due to eczema and rashes.

DERMATOLOGIST
RECOMMENDED
Shea butter, Ceramides,
Sulphur, free from Parabens,
Steroids, Dyes, Fragrance,
HOMEOPATHIC

150mL
5.07 fl oz